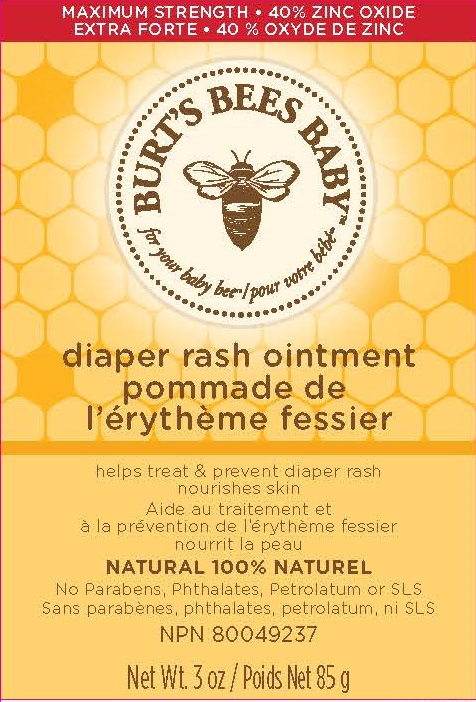 DRUG LABEL: BURTS BEES BABY BEE DIAPER RASH
NDC: 26052-028 | Form: OINTMENT
Manufacturer: BURT'S BEES, INC.
Category: otc | Type: HUMAN OTC DRUG LABEL
Date: 20181221

ACTIVE INGREDIENTS: ZINC OXIDE 40 g/100 g
INACTIVE INGREDIENTS: SHEA BUTTER; CASTOR OIL; JOJOBA OIL; OLIVE OIL; HYDROGENATED CASTOR OIL; CHAMAEMELUM NOBILE FLOWER OIL; LAVANDULA ANGUSTIFOLIA FLOWER; TOCOPHEROL; CALENDULA OFFICINALIS FLOWER; SOYBEAN OIL; CANOLA OIL; ROSEMARY; LAVANDIN OIL; ALMOND OIL; YELLOW WAX; LANOLIN

Baby Bee Diaper Rash Ointment

ACTIVE INGREDIENT

Zinc Oxide 40%

Purpose

Skin Protectant

USES

Helps treat and prevent diaper rash

Protects chafed skin due to diaper rash and helps seal out wetness

WARNINGS

For external use only.

When using this product keep out of eyes.

Stop use and ask a doctor if condition worstened or does not improve after 7 days

Keep out of reach of children. If product is swallowed, get medical help or contact a poison control center right away.

DIRECTIONS

- CHANGE WET AND SOILED DIAPERS PROMPTLY.
- CLEANSE THE DIAPER AREA AND ALLOW TO DRY.
- APPLY OINTMENT LIBERALLY, AS OFTEN AS NECESSARY, WITH EACH DIAPER CHANGE, ESPECIALLY AT BEDTIME OR ANYTIME WHEN EXPOSURE TO WET DIAPERS MAY BE PROLONGED.

INACTIVE INGREDIENTS

PRUNUS AMYGDALUS DULCIS (SWEET ALMOND) OIL, BEESWAX, LANOLIN, RICINUS COMMUNIS (CASTOR) SEED OIL, SIMMONDSIA CHINENSIS (JOJOBA) SEED OIL, BUTYROSPERMUM PARKII (SHEA) BUTTER, GLYCERYL ROSINATE, OLEA EUROPAEA (OLIVE) FRUIT OIL, HYDROGENATED CASTOR OIL, OLEA EUROPAEA (OLIVE) OIL UNSAPONIFIABLES, ANTHEMIS NOBILIS FLOWER OIL, LAVANDULA ANGUSTIFOLIA (LAVENDER) FLOWER, LAVANDULA HYBRIDA OIL, CALENDULA OFFICINALIS FLOWER EXTRACT, ROSMARINUS OFFICINALIS (ROSEMARY) LEAF EXTRACT, TOCOPHEROL, GLYCINE SOJA (SOYBEAN) OIL, CANOLA OIL

OTHER INFORMATION

STORE AT ROOM TEMPERATURE

PACKAGE LABEL

MAXIMUM STRENGTH - 40% ZINC OXIDE

BURT'S BEES

BABY BEE

DIAPER RASH OINTMENT

HELPS TREAT & PREVENT DIAPER RASH

100% NATURAL

NET WT. 3 oz. / 85 g